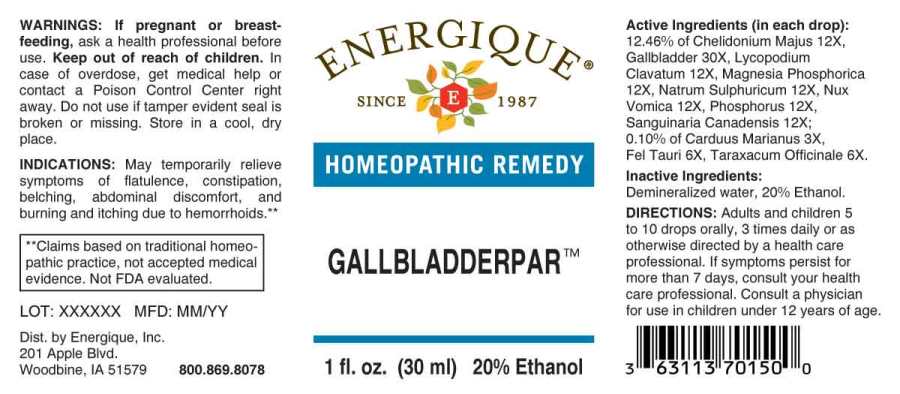 DRUG LABEL: Gallbladderpar
NDC: 44911-0256 | Form: LIQUID
Manufacturer: Energique, Inc.
Category: homeopathic | Type: HUMAN OTC DRUG LABEL
Date: 20230927

ACTIVE INGREDIENTS: MILK THISTLE 3 [hp_X]/1 mL; BOS TAURUS BILE 6 [hp_X]/1 mL; TARAXACUM OFFICINALE 6 [hp_X]/1 mL; CHELIDONIUM MAJUS WHOLE 12 [hp_X]/1 mL; LYCOPODIUM CLAVATUM SPORE 12 [hp_X]/1 mL; MAGNESIUM PHOSPHATE, DIBASIC TRIHYDRATE 12 [hp_X]/1 mL; SODIUM SULFATE 12 [hp_X]/1 mL; STRYCHNOS NUX-VOMICA SEED 12 [hp_X]/1 mL; PHOSPHORUS 12 [hp_X]/1 mL; SANGUINARIA CANADENSIS ROOT 12 [hp_X]/1 mL; SUS SCROFA GALLBLADDER 30 [hp_X]/1 mL
INACTIVE INGREDIENTS: WATER; ALCOHOL

DRUG FACTS:

ACTIVE INGREDIENTS:

(in each drop): 12.46% of Chelidonium Majus 12X, Gallbladder (Suis) 30X, Lycopodium Clavatum 12X, Magnesia Phosphorica 12X, Natrum Sulphuricum 12X, Nux Vomica 12X, Phosphorus 12X, Sanguinaria Canadensis 12X; 0.10% of Carduus Marianus 3X, Fel Tauri 6X, Taraxacum Officinale 6X.

INDICATIONS:

May temporarily relieve symptoms of flatulence, constipation, belching, abdominal discomfort, and burning and itching due to hemorrhoids.**

**Claims based on traditional homeopathic practice, not accepted medical evidence. Not FDA evaluated.

WARNINGS:

If pregnant or breast-feeding, ask a health professional before use.

Keep out of reach of children. In case of overdose, get medical help or contact a Poison Control Center right away.

Do not use if tamper evident seal is broken or missing. Store in a cool, dry place.

KEEP OUT OF REACH OF CHILDREN:

In case of overdose, get medical help or contact a Poison Control Center right away.

DIRECTIONS:

Adults and children 5 to 10 drops orally, 3 times daily or as otherwise directed by a health care professional. If symptoms persist for more than 7 days, consult your health care professional. Consult a physician for use in children under 12 years of age.

INDICATIONS:

May temporarily relieve symptoms of flatulence, constipation, belching, abdominal discomfort, and burning and itching due to hemorrhoids.**

**Claims based on traditional homeopathic practice, not accepted medical evidence. Not FDA evaluated.

INACTIVE INGREDIENTS:

Demineralized water, 20% Ethanol.

QUESTIONS:

Dist. by Energique, Inc.

201 Apple Blvd

Woodbine, IA 51579 800.869.8078

PACKAGE LABEL DISPLAY:

ENERGIQUE

SINCE 1987

HOMEOPATHIC REMEDY

GALLBLADDERPAR

1 fl. oz. (30 ml)